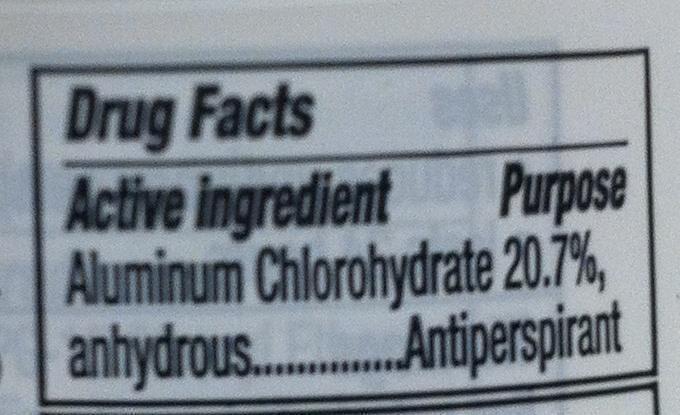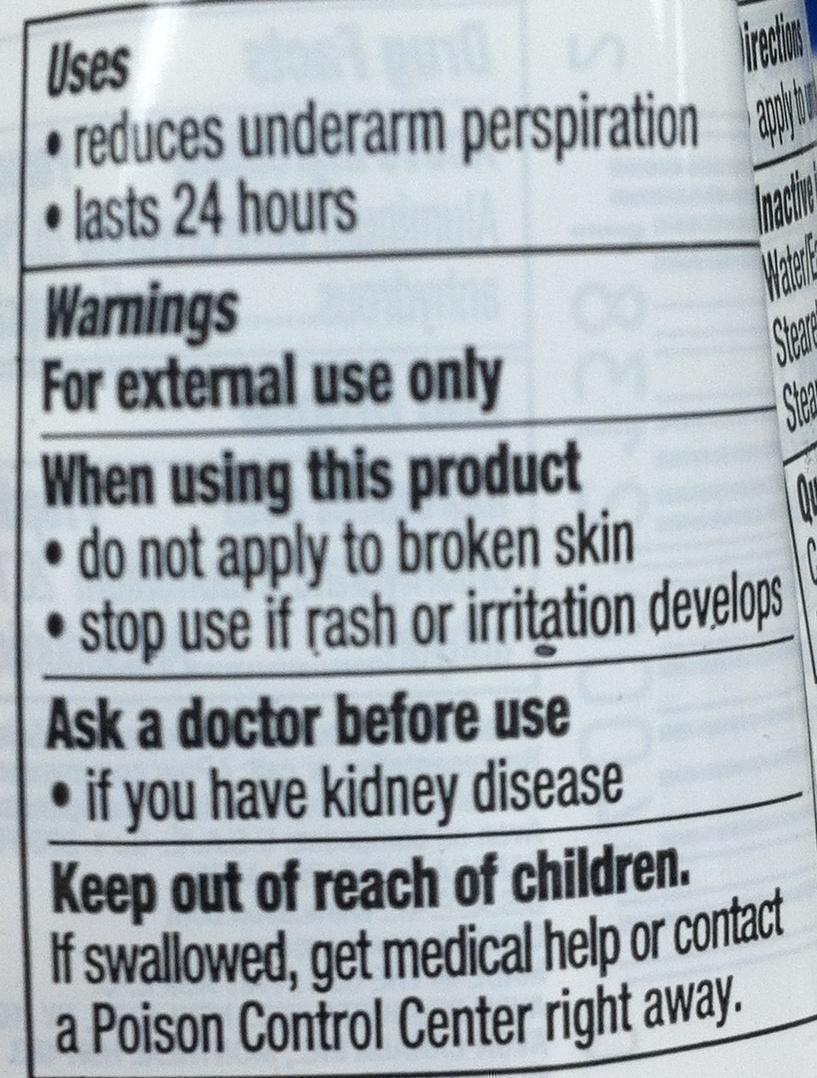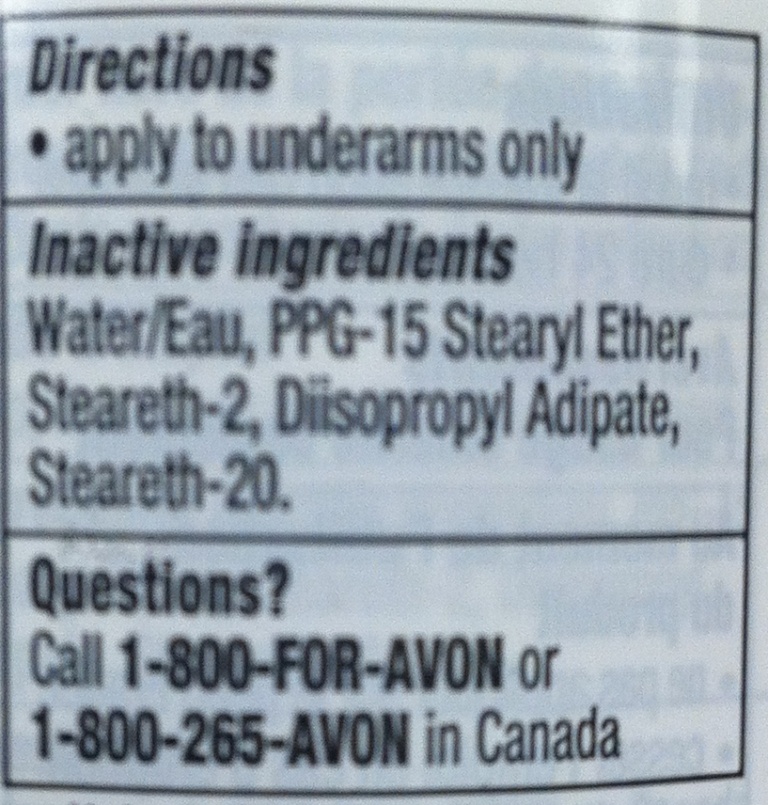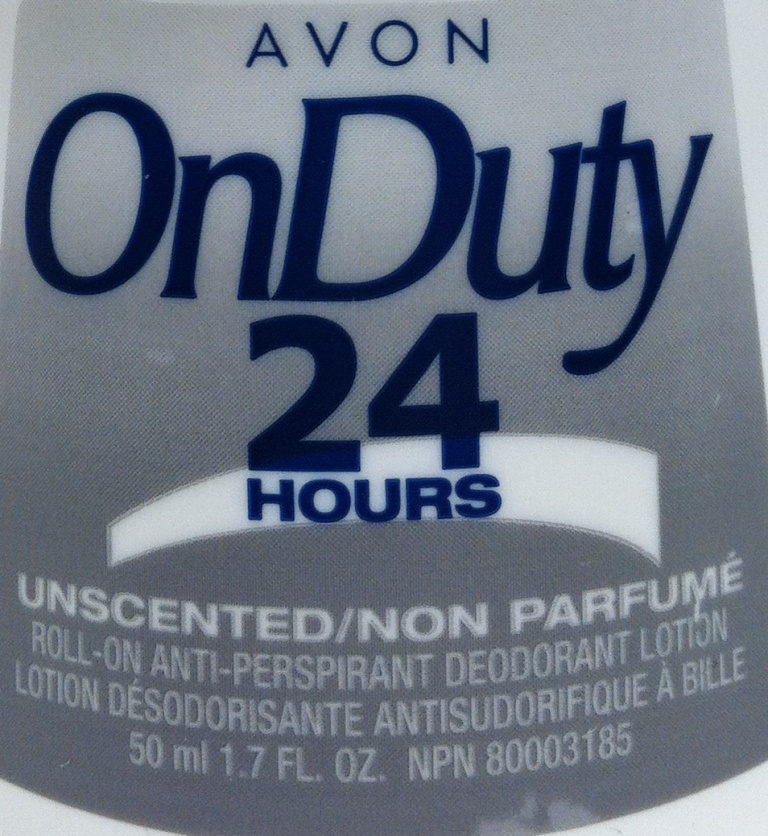 DRUG LABEL: On Duty Unscented
NDC: 10096-5219 | Form: GEL
Manufacturer: New Avon LLC
Category: otc | Type: HUMAN OTC DRUG LABEL
Date: 20190101

ACTIVE INGREDIENTS: ALUMINUM CHLOROHYDRATE 207 mg/1 mL
INACTIVE INGREDIENTS: WATER

On Duty Anti-Perspirant Roll-On Deodorant (Unscented)

Active ingredient

Aluminum Chlorohydrate 20.7%, anhydrous........

Purpose

........Antiperspirant

Uses

- reduces underarm perspiration
- lasts 24 hours

Warnings

For external use only

When using this product

- do not apply to broken skin
- stop use if rash or irritation develops

Ask a doctor before use

- if you have kidney disease

Directions

- apply to underarms only

Inactive ingredients

Water/Eau, PPG-15 Stearyl Ether, Steareth-2, Diisopropyl Adipate, Steareth-20.

Questions?

Call 1-800-FOR-AVON or 1-800-265-AVON in Canada